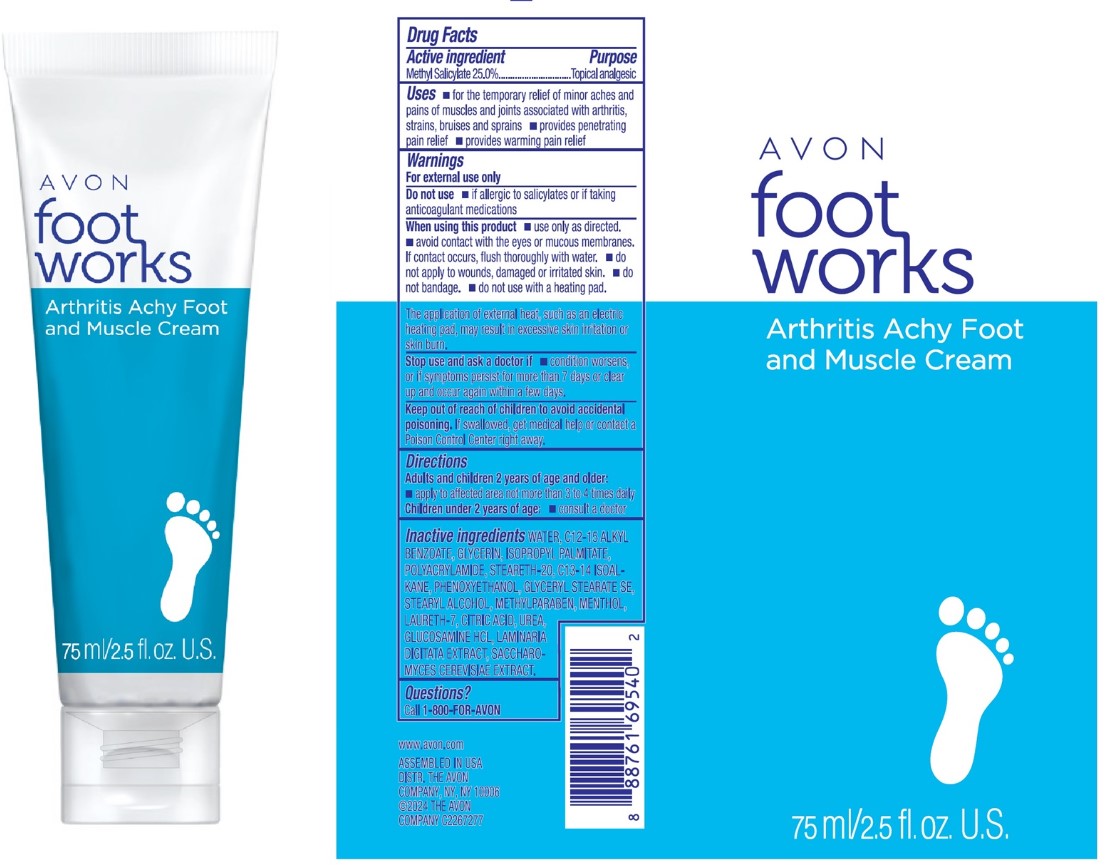 DRUG LABEL: AVON Foot Works Arthritis Achy Foot and Muscle
NDC: 68577-194 | Form: CREAM
Manufacturer: COSMAX USA, CORPORATION
Category: otc | Type: HUMAN OTC DRUG LABEL
Date: 20241220

ACTIVE INGREDIENTS: METHYL SALICYLATE 25 mg/1 g
INACTIVE INGREDIENTS: POLYACRYLAMIDE (10000 MW); WATER; C12-15 ALKYL BENZOATE; STEARETH-20; METHYLPARABEN; MENTHOL; UREA; GLYCERIN; PHENOXYETHANOL; ISOPROPYL PALMITATE; C13-14 ISOPARAFFIN; GLYCERYL STEARATE SE; STEARYL ALCOHOL; LAURETH-7; CITRIC ACID; GLUCOSAMINE HYDROCHLORIDE; LAMINARIA DIGITATA; SACCHAROMYCES CEREVISIAE

AVON Foot works Arthritis Achy Foot and Muscle Cream

Active Ingredient

Methyl Salicylate 25.0%

Purpose

Topical analgesic

USES

- for the temporary relief of minor aches and pains of muscles and joints associated with arthritis, strains, bruises and sprains
- provides penetrating pain relief
- provides warming pain relief

Warnings

For external use only

Do not use if allergic to salicylates of if taking anticoagulant medications

When using this product

- use only as directed.
- avoid contact with the eyes or mucous membrances. If contact occurs, flush thoroughly with water.
- do not apply to wounds, damaged or irritated skin.
- do not bandage.
- do not use with a heating pad.

Stop use and ask a doctor if

- condition worsens, or if symptoms persist for more than 7 days or clear up and occur again within a few days.

Keep out of reach of children to avoid accidental poisoning.

If swallowed, get medical help or contact a Poison Control Center right away.

DIRECTIONS

Adults and children 2 years of age and older:

- apply to affected area not more than 3 to 4 times daily

Children under 2 years of age:

- consult a doctor

Inactive Ingredients

Water, C12-15 Alkyl Benzoate, Glycerin, Isopropyl Palmitate, Polyacrylamide, Steareth-20, C13-14 Isoalkane, Phenoxyethanol, Glyceryl Stearate SE, Stearyl Alcohol, Methylparaben, Menthol, Laureth-7, Citric Acid, Urea, Glucosamine HCl, Laminaria Digitata Extract, Saccharomyces Cerevisiae Extract